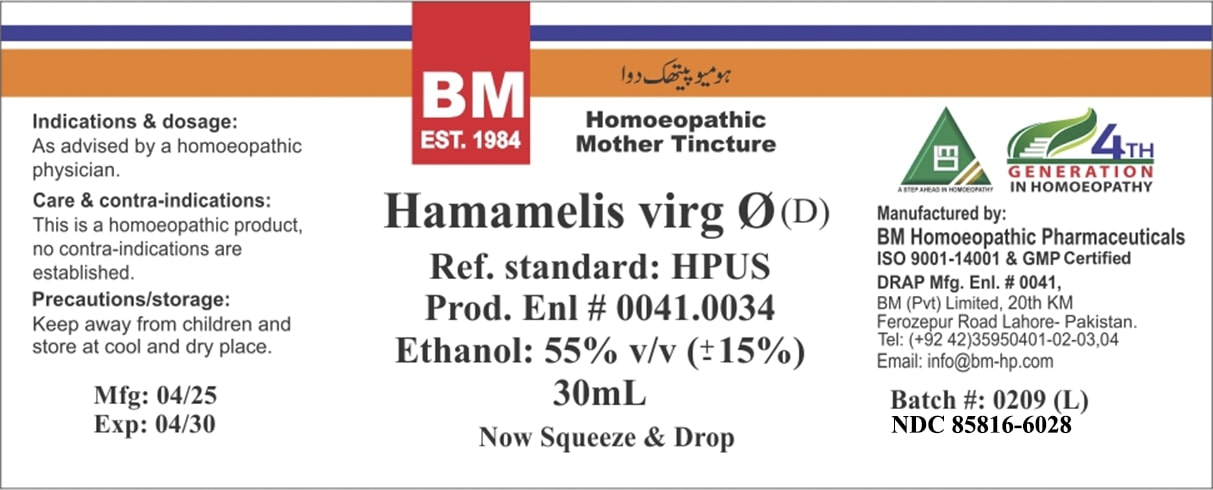 DRUG LABEL: BM Hamamelis Virgiana
NDC: 85816-6028 | Form: TINCTURE
Manufacturer: BM Private Limited
Category: homeopathic | Type: HUMAN OTC DRUG LABEL
Date: 20250627

ACTIVE INGREDIENTS: HAMAMELIS VIRGINIANA ROOT BARK/STEM BARK 1 [hp_X]/1 mL
INACTIVE INGREDIENTS: WATER 0.4 mL/1 mL; PROPYLENE GLYCOL 0.02 mL/1 mL; ALCOHOL 0.635 mL/1 mL

BM Hamamelis Virgiana tincture

ACTIVE INGREDIENT

Hamamelis Virgiana

INACTIVE INGREDIENT

purified water, alcohol and propylene glycol

PURPOSE

Indications & dosage: As advised by a homoeopathic physician.

Indications & dosage: As advised by a homoeopathic physician.

Indications & dosage: As advised by a homoeopathic physician.

CONTRAINDICATIONS

Care & contra-indications: This is a homoeopathic product, no contra-indications are established.

WARNINGS

Precautions/storage: Keep away from children and store at cool and dry place.

KEEP OUT OF REACH OF CHILDREN

Precautions/storage: Keep away from children and store at cool and dry place.

STORAGE AND HANDLING

Precautions/storage: Keep away from children and store at cool and dry place.

Entire package label